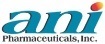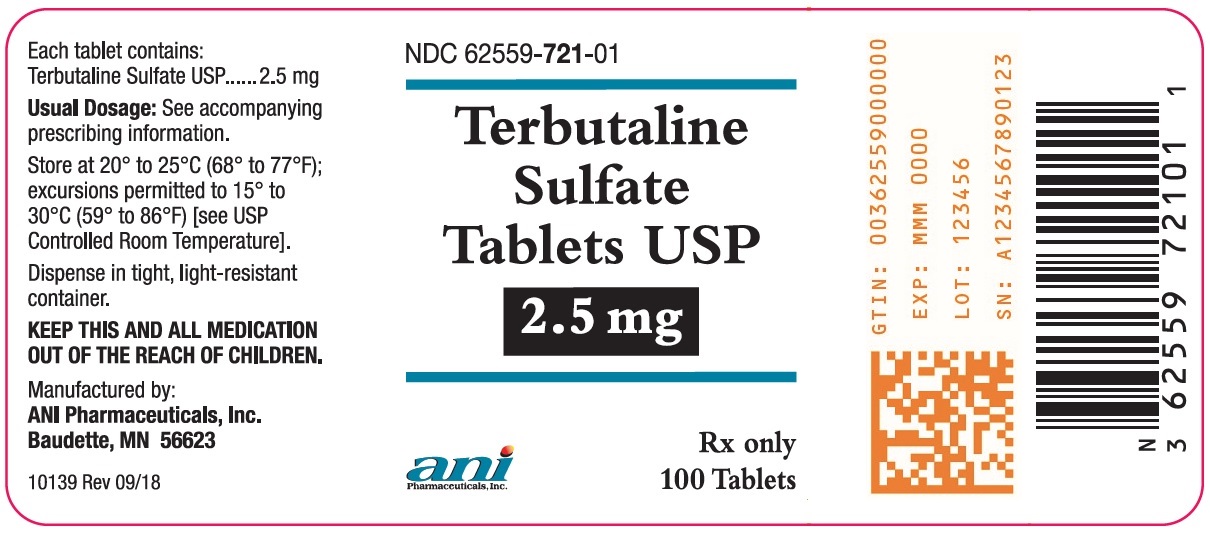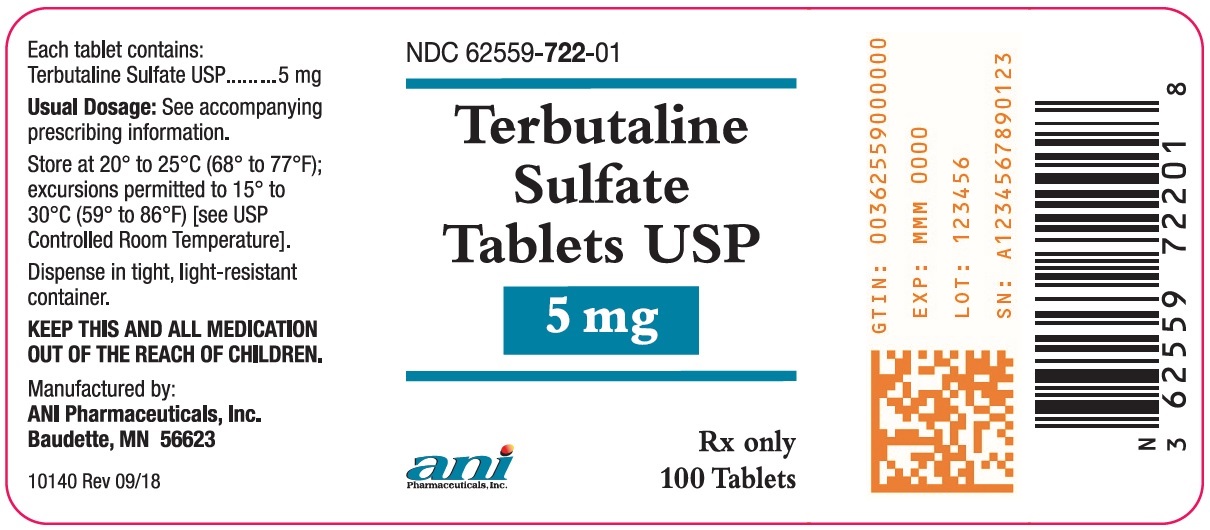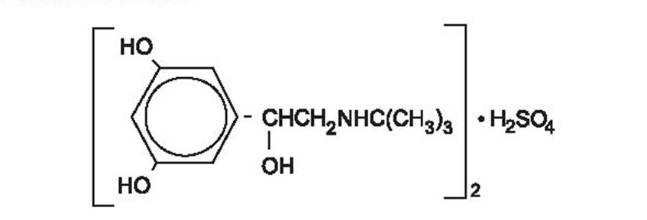 DRUG LABEL: Terbutaline Sulfate
NDC: 62559-721 | Form: TABLET
Manufacturer: ANI Pharmaceuticals, Inc.
Category: prescription | Type: HUMAN PRESCRIPTION DRUG LABEL
Date: 20191115

ACTIVE INGREDIENTS: TERBUTALINE SULFATE 2.5 mg/1 1
INACTIVE INGREDIENTS: LACTOSE MONOHYDRATE; STARCH, CORN; MICROCRYSTALLINE CELLULOSE; MAGNESIUM STEARATE; POVIDONE K30

Terbutaline Sulfate Tablets USP
Rx only

DESCRIPTION

Terbutaline sulfate USP, the active ingredient of Terbutaline Sulfate Tablets USP, is a beta-adrenergic agonist bronchodilator available as tablets of 2.5 mg (2.05 mg of the free base) and 5 mg (4.1 mg of the free base) for oral administration. Terbutaline sulfate is ±-α-[(tert-butylamino)methyl]-3,5-dihydroxybenzyl alcohol sulfate (2:1) (salt). The empirical formula is (C12H19NO3)2• H2SO4 and the structural formula is:

Terbutaline sulfate USP is a white to gray-white crystalline powder. It is odorless or has a faint odor of acetic acid. It is soluble in water and in 0.1N hydrochloric acid, slightly soluble in methanol, and insoluble in chloroform. Its molecular weight is 548.65.

Inactive Ingredients: Microcrystalline cellulose, lactose monohydrate, magnesium stearate, povidone, and corn starch.

WARNING: TOCOYSIS

Oral terbutaline sulfate has not been approved for and should not be used for acute or maintenance tocolysis. In particular, terbutaline sulfate should not be used for maintenance tocolysis in the outpatient or home setting.

During pregnancy, serious adverse reactions, including death, have been reported after administration of terbutaline sulfate to pregnant women. In the mother, these adverse reactions include increased heart rate, transient hyperglycemia, hypokalemia, cardiac arrhythmias, pulmonary edema and myocardial ischemia. Increased fetal heart rate and neonatal hypoglycemia may occur as a result of maternal administration. [See Contraindications-Tocolysis]

CLINICAL PHARMACOLOGY

In vitro and in vivo pharmacologic studies have demonstrated that terbutaline exerts a preferential effect on beta2-adrenergic receptors. While it is recognized that beta2-adrenergic receptors are the predominant receptors in bronchial smooth muscle, data indicate that there is a population of beta2-receptors in the human heart, existing in a concentration between 10% to 50%. The precise function of these receptors has not been established [see Warnings]. In controlled clinical studies in patients given terbutaline sulfate orally, proportionally greater changes occurred in pulmonary function parameters than in heart rate or blood pressure. While this suggests a relative preference for the beta2-receptors in man, the usual cardiovascular effects commonly associated with other sympathomimetic agents were also observed with terbutaline sulfate.

The pharmacologic effects of beta-adrenergic agonists, including terbutaline, are at least in part attributable to stimulation through beta-adrenergic receptors of intracellular adenyl cyclase, the enzyme which catalyzes the conversion of adenosine triphosphate (ATP) to cyclic 3', 5'-adenosine monophosphate (cAMP). Increased cAMP levels are associated with relaxation of bronchial smooth muscle and inhibition of release of mediators of immediate hypersensitivity from cells, especially from mast cells.

Controlled clinical studies have shown that terbutaline sulfate relieves bronchospasm in chronic obstructive pulmonary disease by significantly increasing pulmonary function (e.g., an increase of 15% or more in FEV1 and in FEF25%-75%). After administration of terbutaline sulfate tablets, a measurable change in flow rate usually occurs within 30 minutes, and a clinically significant improvement in pulmonary function occurs within 60 to 120 minutes. The maximum effect usually occurs within 120 to 180 minutes. Terbutaline sulfate also produces a clinically significant decrease in airway and pulmonary resistance, which persists for 4 hours or longer. Significant bronchodilator action (as measured by airway resistance, FEF25%-75% or PEFR) has also been demonstrated for up to 8 hours in some studies.

In studies comparing the effectiveness of terbutaline sulfate with that of ephedrine for up to 3 months, both drugs maintained a significant improvement in pulmonary function throughout this period of treatment.

Preclinical

Studies in laboratory animals (minipigs, rodents, and dogs) have demonstrated the occurrence of cardiac arrhythmias and sudden death (with histologic evidence of myocardial necrosis) when beta-agonists and methylxanthines were administered concurrently. The clinical significance of these findings is unknown.

Pharmacokinetics

Oral administration of 5 mg terbutaline sulfate tablets or 5 mg terbutaline sulfate in solution in 17 healthy, adult, male subjects, resulted in mean (SD) peak plasma terbutaline concentration of 8.3 (3.9) and 8.6 (3.6) ng/mL, which were observed at median (range) times of 2 (1 to 3) and 1.5 (0.5 to 3.0) hours after dosing. The mean (SD) AUC (0 to 48) values were 54.6 (26.8) and 53.1 (23.5) hr•ng/mL, and corresponded to a bioavailability of 103% for the tablet relative to the solution.

After oral administration of terbutaline, 51 to 62 mcg/kg of body weight, to 3 healthy male subjects, peak serum levels of 3.1 to 6.2 ng/mL were observed 1 to 3 hours later. In the same study, after 3 days only 30% to 50% of the dose was recovered from urine and the remainder from the feces, which may indicate poor absorption.

After an oral dose to asthmatic patients, the elimination half-life of terbutaline was approximately 3.4 hours.

In comparison to oral dosing, subcutaneous administration of 0.5 mg of terbutaline sulfate to 17 healthy, adult, male subjects resulted in a mean (SD) peak plasma terbutaline concentration of 9.6 (3.6) ng/mL, which was observed at a median (range) time of 0.5 (0.08 to 1.0) hours after dosing. The mean (SD) AUC (0 to 48) and total body clearance values were 29.4 (14.2) hr•ng/mL, and 311 (112) mL/min, respectively. The terminal half-life was determined in 9 of the 17 subjects and had a mean (SD) of 5.7 (2.0) hours.

About 90% of the drug was excreted in the urine at 96 hours after subcutaneous administration, with about 60% of this being unchanged drug. The sulfate conjugate is a major metabolite of terbutaline, and urinary excretion is the primary route of elimination.

There are no reports of any clinical pharmacokinetic studies investigating dose proportionality, effect of food, or special population studies with terbutaline.

INDICATIONS AND USAGE

Terbutaline Sulfate Tablets USP are indicated for the prevention and reversal of bronchospasm in patients 12 years of age and older with asthma and reversible bronchospasm associated with bronchitis and emphysema.

CONTRAINDICATIONS

1. Tocolysis

Oral terbutaline sulfate is contraindicated for the treatment of acute or maintenance tocolysis [see Boxed Warning: Tocolysis].

2. Hypersensitivity

Terbutaline sulfate is contraindicated in patients known to be hypersensitive to sympathomimetic amines or any component of this drug product.

WARNINGS

Deterioration of Asthma

Asthma may deteriorate acutely over a period of hours or chronically over several days or longer. If the patient needs more doses of terbutaline sulfate tablets than usual, this may be a marker of destabilization of asthma and requires reevaluation of the patient and the treatment regimen, giving special consideration to the possible need for anti-inflammatory treatment, e.g., corticosteroids.

Use of Anti-Inflammatory Agents

The use of beta-adrenergic agonist bronchodilators alone may not be adequate to control asthma in many patients. Early consideration should be given to adding anti-inflammatory agents, e.g., corticosteroids.

Cardiovascular Effects

Terbutaline sulfate, like all other beta-adrenergic agonists, can produce a clinically significant cardiovascular effect in some patients as measured by pulse rate, blood pressure, and/or symptoms. Although such effects are uncommon after administration of terbutaline sulfate tablets at recommended doses, if they occur, the drug may need to be discontinued. In addition, beta-agonists have been reported to produce electrocardiogram (ECG) changes, such as flattening of the T wave, prolongation of the QTc interval, and ST segment depression. The clinical significance of these findings is unknown. Therefore, terbutaline sulfate tablets, like all sympathomimetic amines, should be used with caution in patients with cardiovascular disorders, especially coronary insufficiency, cardiac arrhythmias, and hypertension.

Seizures

There have been rare reports of seizures in patients receiving terbutaline; seizures did not recur in these patients after the drug was discontinued.

PRECAUTIONS

General

Terbutaline, as with all sympathomimetic amines, should be used with caution in patients with cardiovascular disorders, including ischemic heart disease, hypertension, and cardiac arrhythmias; hyperthyroidism; diabetes mellitus; hypersensitivity to sympathomimetic amines; and convulsive disorders. Significant changes in systolic and diastolic blood pressure have been seen and could be expected to occur in some patients after use of any beta-adrenergic bronchodilator.

Immediate hypersensitivity reactions and exacerbation of bronchospasm have been reported after terbutaline administration.

Beta-adrenergic agonist medications may produce significant hypokalemia in some patients, possibly through intracellular shunting, which has the potential to produce adverse cardiovascular effects. The decrease is usually transient, not requiring supplementation.

Large doses of intravenous terbutaline sulfate have been reported to aggravate preexisting diabetes and ketoacidosis.

Information for Patients

The action of terbutaline sulfate tablets should last up to 6 hours or longer. Terbutaline sulfate tablets should not be used more frequently than recommended. Do not increase the dose or frequency of terbutaline sulfate tablets without consulting your physician. If you find that treatment with terbutaline sulfate tablets becomes less effective for symptomatic relief, your symptoms become worse, and/or you need to use the product more frequently than usual, you should seek medical attention immediately. While taking terbutaline sulfate tablets, other inhaled drugs and asthma medications should be taken only as directed by your physician. Common adverse effects include palpitations, chest pain, rapid heart rate, tremor or nervousness. If you are pregnant or nursing, contact your physician about use of terbutaline sulfate tablets. Effective and safe use of terbutaline sulfate tablets includes an understanding of the way that it should be administered.

Drug Interactions

The concomitant use of terbutaline sulfate tablets with other sympathomimetic agents is not recommended, since the combined effect on the cardiovascular system may be deleterious to the patient. However, this does not preclude the use of an aerosol bronchodilator of the adrenergic-stimulant type for the relief of an acute bronchospasm in patients receiving chronic oral therapy with terbutaline sulfate tablets.

Monoamine Oxidase Inhibitors and Tricyclic Antidepressants

Terbutaline sulfate should be administered with extreme caution to patients being treated with monoamine oxidase inhibitors or tricyclic antidepressants, or within 2 weeks of discontinuation of such agents, since the action of terbutaline sulfate on the vascular system may be potentiated.

Beta-Blockers

Beta-adrenergic receptor blocking agents not only block the pulmonary effect of beta-agonists, such as terbutaline sulfate, but may produce severe bronchospasm in asthmatic patients. Therefore, patients with asthma should not normally be treated with beta-blockers. However, under certain circumstances, e.g., as prophylaxis after myocardial infarction, there may be no acceptable alternatives to the use of beta-adrenergic blocking agents in patients with asthma. In this setting, cardioselective beta-blockers could be considered, although they should be administered with caution.

Diuretics

The ECG changes and/or hypokalemia that may result from the administration of non-potassium sparing diuretics (such as loop or thiazide diuretics) can be acutely worsened by beta-agonists, especially when the recommended dose of the beta-agonist is exceeded. Although the clinical significance of these effects is not known, caution is advised in the co-administration of beta-agonists with non-potassium sparing diuretics.

Carcinogenesis, Mutagenesis, and Impairment of Fertility

In a 2-year study in Sprague-Dawley rats, terbutaline sulfate caused a significant and dose-related increase in the incidence of benign leiomyomas of the mesovarium at dietary doses of 50 mg/kg, and above (approximately 25 times the maximum recommended daily oral dose for adults on a mg/m^2 basis). In a 21-month study in CD-1 mice, terbutaline sulfate showed no evidence of tumorigenicity at dietary doses up to 200 mg/kg (approximately 55 times the maximum recommended daily oral dose for adults on a mg/m^2 basis). The mutagenicity potential of terbutaline sulfate has not been determined. Reproduction studies in rats using terbutaline sulfate demonstrated no impairment of fertility at oral doses up to 50 mg/kg (approximately 25 times the maximum recommended daily oral dose for adults on a mg/m^2 basis).

Teratogenic Effects

There are no adequate and well-controlled studies of terbutaline sulfate in pregnant women. Published animal studies show that rat offspring exhibit alterations in behavior and brain development, including decreased cellular proliferation and differentiation when dams were treated subcutaneously with terbutaline during the late stage of pregnancy and lactation period. Terbutaline exposures in rat dams were approximately 6.5 times the common human dose in adults of 15 mg/day, on a mg/m^2 basis.

Oral terbutaline sulfate has not been approved for and should not be used for acute or maintenance tocolysis. In particular, terbutaline sulfate should not be used for tocolysis in the outpatient or home setting. Serious adverse reactions, including death, have been reported after administration of terbutaline sulfate to pregnant women. In the mother, these adverse reactions include increased heart rate, transient hyperglycemia, hypokalemia, cardiac arrhythmias, pulmonary edema and myocardial ischemia. Increased fetal heart rate and neonatal hypoglycemia may occur as a result of maternal administration [see Boxed Warning: Tocolysis and Contraindications-Tocolysis]

In animal embryofetal developmental studies, no teratogenic effects were observed in offspring when pregnant rats and rabbits received terbutaline sulfate at oral doses up to 50 mg/kg/day, approximately 32 and 65 times, respectively, the maximum recommended daily oral dose for adults, on a mg/m^2 basis.

Terbutaline sulfate should be used during pregnancy only if the potential benefit justifies the potential risk to the fetus.

Use in Labor and Delivery

Because of the potential for beta-agonist interference with uterine contractility, use of terbutaline sulfate tablets for relief of bronchospasm during labor should be restricted to those patients in whom the benefits clearly outweigh the risk.

Terbutaline crosses the placenta. After single dose IV administration of terbutaline to 22 women in late pregnancy who were delivered by elective Cesarean section due to clinical reasons, umbilical blood levels of terbutaline were found to range from 11% to 48% of the maternal blood levels.

Nursing Mothers

It is not known whether this drug is excreted in human milk. Therefore, terbutaline sulfate tablets should be used during nursing only if the potential benefit justifies the possible risk to the newborn.

Pediatric Use

Terbutaline sulfate tablets are not recommended for patients under the age of 12 years because of insufficient clinical data to establish safety and effectiveness [see Dosage and Administration].

Geriatric Use

Clinical studies of terbutaline sulfate did not include sufficient numbers of subjects aged 65 and over to determine whether they respond differently from younger subjects. Other reported clinical experience has not identified differences in responses between the elderly and younger patients. In general, dose selection for an elderly patient should be cautious, usually starting at the low end of the dosing range, reflecting the greater frequency of decreased hepatic, renal, or cardiac function, and of concomitant disease or other drug therapy.

ADVERSE REACTIONS

Adverse reactions observed with terbutaline sulfate are similar to those commonly seen with other sympathomimetic amines. All of these reactions are generally transient in nature and usually do not require treatment. The frequency of these side effects appears to diminish with continued therapy.

The following table lists the adverse reactions seen in 199 patients treated with terbutaline sulfate tablets during six double-blind crossover studies and four double-blind parallel studies (short- and long-term) performed in the United States.

Percent Incidence of Adverse Reactions
(Total Daily Dosage Range 5 to 15 mg)
Terbutaline N=199
Reaction | %
Nervous System
Nervousness | 35.0
Tremor | 15.0
Somnolence | 5.5
Dizziness | 3.5
Anxiety | 1.0
Insomnia | 1.5
Cardiovascular
Palpitations | 5.0
Tachycardia | 3.5
Extrasystoles ventricular | 1.5
Vasodilations | 1.0
Digestive
Nausea | 3.0
Dry mouth | 1.5
Body as a Whole
Headache | 7.5
Asthenia | 2.0
Skin and Appendages
Sweating | 1.0

The following adverse reactions each occurred in fewer than 1% of patients: hallucinations, rash, paresthesia, hypertonia, (muscle cramps), vomiting.

There have been rare reports of elevations in liver enzymes and of hypersensitivity vasculitis.

To report SUSPECTED ADVERSE REACTIONS, contact ANI Pharmaceuticals, Inc. at 1-800-308-6755 or FDA at 1-800-FDA-1088 or www.fda.gov/medwatch.

DOSAGE AND ADMINISTRATION

Adults

The usual oral dose of terbutaline sulfate tablets for adults is 5 mg administered at approximately six-hour intervals, three times daily, during the hours the patient is usually awake. If side effects are particularly disturbing, the dose may be reduced to 2.5 mg three times daily, and still provide a clinically significant improvement in pulmonary function. The total dose within 24 hours should not exceed 15 mg.

Children

Terbutaline sulfate tablets are not recommended for use in children below the age of 12 years. A dosage of 2.5 mg three times daily is recommended for children 12 to 15 years of age. The total dose within 24 hours should not exceed 7.5 mg.

If a previously effective dosage regimen fails to provide the usual relief, medical advice should be sought immediately as this is often a sign of seriously worsening asthma that would require reassessment of therapy.

OVERDOSAGE

The median subcutaneous lethal dose of terbutaline sulfate in mature rats is approximately 165 mg/kg (approximately 90 times the maximum recommended daily oral dose for adults on a mg/m^2 basis). The median subcutaneous lethal dose of terbutaline sulfate in young rats is approximately 2000 mg/kg (approximately 1100 times the maximum recommended daily oral dose for adults on a mg/m2 basis).

The expected symptoms with overdosage are those of excessive beta-adrenergic stimulation and/or occurrence or exaggeration of any of the symptoms listed under ADVERSE REACTIONS, e.g., seizures, angina, hypertension or hypotension, tachycardia with rates up to 200 beats per minute, arrhythmias, nervousness, headache, tremor, dry mouth, palpitation, nausea, dizziness, fatigue, malaise, and insomnia. Hypokalemia may also occur.

There is no specific antidote. Treatment consists of discontinuation of terbutaline sulfate tablets together with appropriate symptomatic therapy. The judicious use of a cardioselective beta-receptor blocker may be considered, bearing in mind that such medication can produce bronchospasm. There is insufficient evidence to determine if dialysis is beneficial for overdosage of terbutaline sulfate.

In the alert patient who has taken excessive oral medication, the stomach should be emptied by induced emesis followed by lavage. In the unconscious patient, the airway should be secured with a cuffed endotracheal tube before lavage, and emesis should not be induced. Instillation of activated charcoal slurry may help reduce absorption of terbutaline. Adequate respiratory exchange should be maintained, and cardiac and respiratory support provided as needed. The patient should be monitored until signs and symptoms of overdosage have subsided.

HOW SUPPLIED

Terbutaline Sulfate Tablets USP are available as:

2.5 mg: White to faintly yellow, oval, biconvex tablets debossed with ‘ANI’ and ‘721’ on one side and bisected on the reverse side. They are packaged in high density polyethylene (HDPE) bottles of 100 tablets (NDC 62559-721-01).

5 mg: White to faintly yellow, round, biconvex tablets debossed with ‘ANI’ and ‘722’ on one side and bisected on the reverse side. They are packaged in high density polyethylene (HDPE) bottles of 100 tablets (NDC 62559-722-01).

Store at 20° to 25°C (68° to 77°F); excursions permitted to 15° to 30°C (59° to 86°F) [see USP Controlled Room Temperature].
Dispense in tight, light-resistant container (as defined in the USP).

Manufactured by:
ANI Pharmaceuticals, Inc.
Baudette, MN 56623

10141 Rev 09/18

PACKAGE/LABEL PRINCIPAL DISPLAY PANEL

Terbutaline Sulfate Tablets USP
2.5 mg
NDC 62559-721-01
Rx only
100 Tablets

PACKAGE/LABEL PRINCIPAL DISPLAY PANEL

Terbutaline Sulfate Tablets USP
5 mg
NDC 62559-722-01
Rx only
100 Tablets